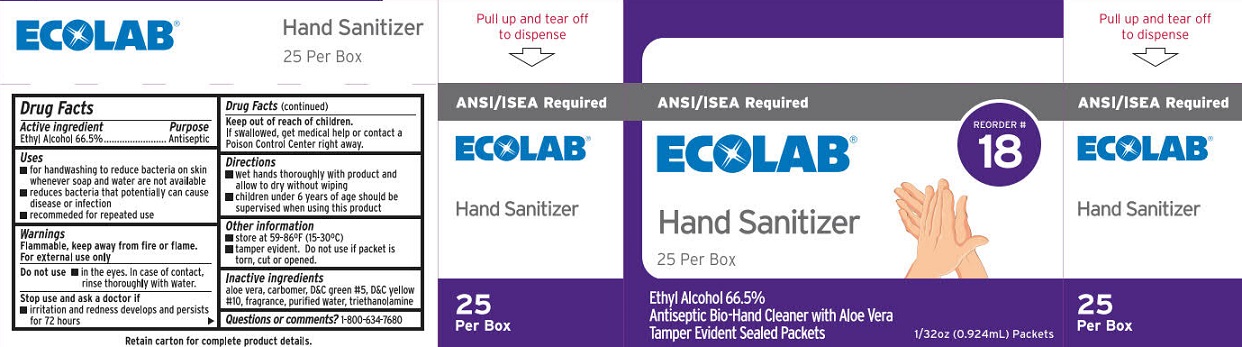 DRUG LABEL: ECOLAB Hand Sanitizer
NDC: 71338-124 | Form: GEL
Manufacturer: ECOLAB Food Safety Specialties, Inc.
Category: otc | Type: HUMAN OTC DRUG LABEL
Date: 20250909

ACTIVE INGREDIENTS: ALCOHOL 540.26 g/1 L
INACTIVE INGREDIENTS: TROLAMINE; CARBOMER INTERPOLYMER TYPE A (ALLYL SUCROSE CROSSLINKED); D&C GREEN NO. 5; D&C YELLOW NO. 10; WATER; ALOE VERA LEAF

ECOLAB Hand Sanitizer

Drug Facts

Active ingredient

Ethyl Alcohol 66.5%

Purpose

Antiseptic

Uses

- for handwashing to reduce bacteria on skin whenever soap and water are not available
- reduces bacteria that potentially can cause disease or infection
- recommended for repeated use

Warnings

Flammable, keep away from fire or flame.

For external use only.

Do not use

- in the eyes. IIn case of contact, rinse thoroughly with water.

Stop use and ask a doctor if

- irritation and redness develop and persists for more than 72 hours.

Keep out of reach of children.

If swallowed, get medical help or contact a Poison Control Center right away.

Directions

- wet hands thoroughly with product and allow to dry without wiping
- children under 6 years of age should be supervised while using this product

Other information

- store at 59-86°F (15-30°C)
- tamper evident. Do not use if packet is torn, cut or opened.

Inactive ingredients

aloe vera, carbomer, D&C green #5, D&C yellow #10, fragrance, purified water, triethanolamine

Questions or comments?

1-800-634-7680

ECOLAB Hand Sanitizer Label

ANSI/ISEA Required

ECOLAB®

Hand Sanitizer

Reorder # 18

25 Per Box

Ethyl Alcohol 66.5%^

Antiseptic Bio-Hand Cleaner

with Aloe Vera

Tamper Evident Sealed Packets

1/32 oz (0.924mL) Packets